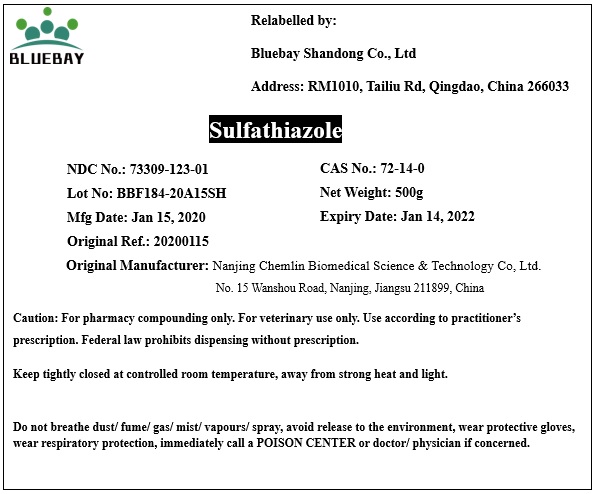 DRUG LABEL: Sulfathiazole
NDC: 73309-123 | Form: POWDER
Manufacturer: BLUEBAY SHANDONG CO.,LTD
Category: other | Type: BULK INGREDIENT
Date: 20200416

ACTIVE INGREDIENTS: SULFATHIAZOLE 1 g/1 g

Sulfathiazole